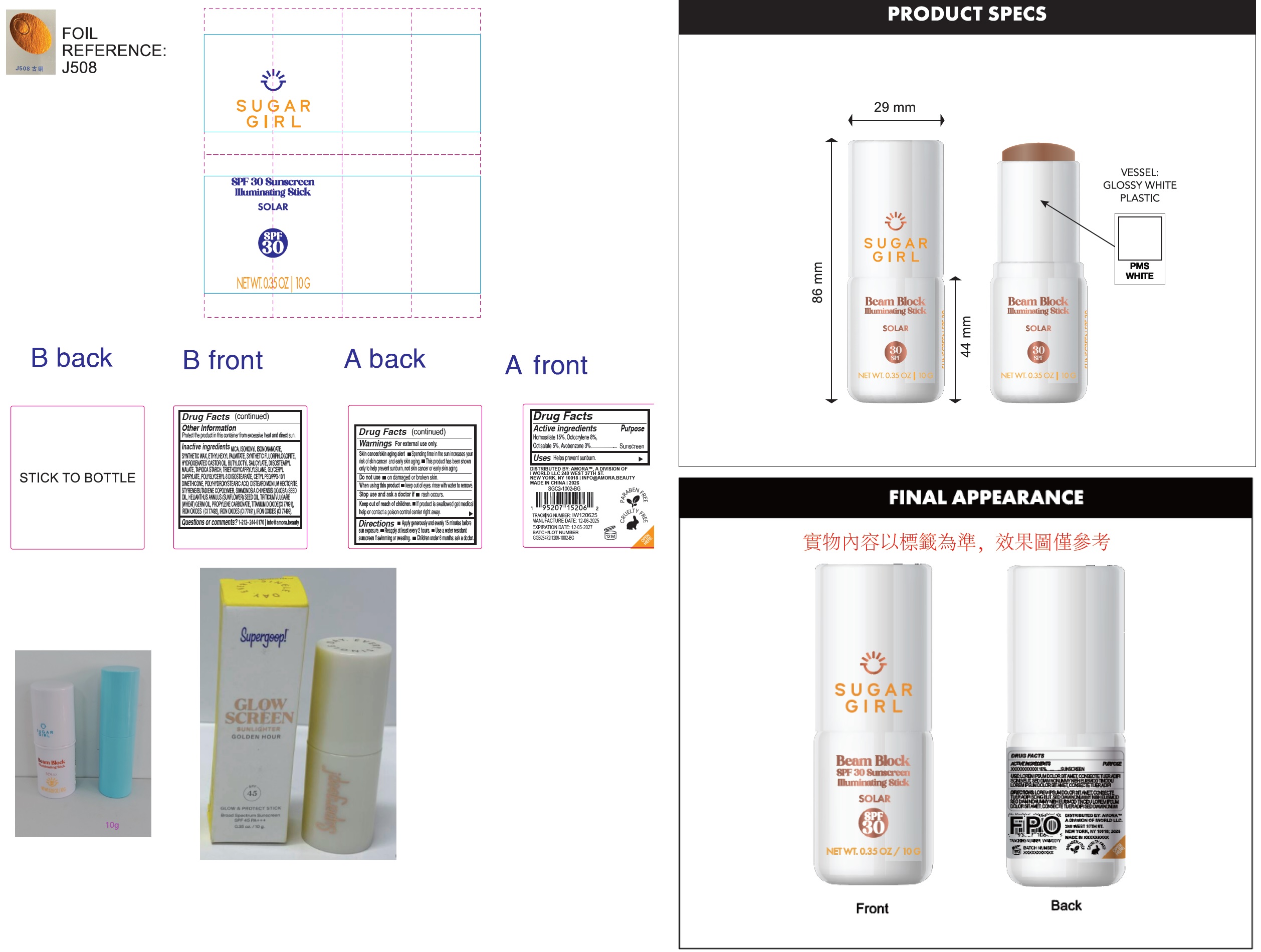 DRUG LABEL: Sugargirl  SPF 30 Sunscreen Illuminating Stick Sunlight
NDC: 85179-048 | Form: STICK
Manufacturer: I World LLC
Category: otc | Type: HUMAN OTC DRUG LABEL
Date: 20260127

ACTIVE INGREDIENTS: HOMOSALATE 150 mg/1 g; OCTOCRYLENE 80 mg/1 g; OCTISALATE 50 mg/1 g; AVOBENZONE 30 mg/1 g
INACTIVE INGREDIENTS: MICA; ISONONYL ISONONANOATE; ETHYLHEXYL PALMITATE; HYDROGENATED CASTOR OIL; MAGNESIUM POTASSIUM ALUMINOSILICATE FLUORIDE; BUTYLOCTYL SALICYLATE; DIISOSTEARYL MALATE; STARCH, TAPIOCA; TRIETHOXYCAPRYLYLSILANE; GLYCERYL MONOCAPRYLATE; POLYGLYCERYL-3 DIISOSTEARATE; DIMETHICONE; DISTEARDIMONIUM HECTORITE; JOJOBA OIL; SUNFLOWER OIL; WHEAT GERM OIL; PROPYLENE CARBONATE; TITANIUM DIOXIDE; FERRIC OXIDE YELLOW; FERRIC OXIDE RED; FERROSOFERRIC OXIDE

Sugargirl SPF 30 Sunscreen Illuminating Stick Sunlight

Active ingredients

Homosalate 15%, Octocrylene 8%, Octisalate 5%, Avobenzone 3%

Purpose

Sunscreen

Uses

Helps prevent sunburn.

Warnings

For external use only.
Skin cancer/skin aging alert

- Spending time in the sun increases your risk of skin cancer and early skin aging.
- This product has been shown only to help prevent sunburn, notskin cancer or early skin aging.

Do not use

- on damaged or broken skin.

when using this product

- keep out of eyes. rinse with water to remove.

Stop use and ask a doctor if

- rash occurs.

Keep out of reach of children.

- If product is swallowed get medical help or contact a poison control centre right away.

Directions

- Apply generously and evenly 15 minutes before sun exposer.
- Reapply at least every 2 hours.
- Use a water resistant sunscreen if swimming or sweating.
- Children under 6 month: ask a doctor.

Other information

Protect the product in this container from excessive heat and direct sun.

Inactive ingredients

MICA, ISONONYL ISONONANOATE, SYNTHETIC WAX, ETHYLHEXYL PALMITATE, HYDROGENATED CASTOR OIL, SYNTHETIC FLUORPHLOGOPITE, BUTYLOCTYL SALICYLATE, DIISOSTEARYL MALATE, TAPIOCA STARCH, TRIETHOXYCAPRYLYLSILANE, GLYCERYL CAPRYLATE, POLYGLYCERYL-3 DIISOSTEARATE, CETYL PEG/PPG-10/1 DIMETHICONE, DIMETHICONE, POLYHYDROXYSTEARIC ACID, DISTEARDIMONIUM HECTORITE, SIMMONDSIA CHINENSIS (JOJOBA) SEED OIL, HELIANTHUS ANNUUS (SUNFLOWER) SEED OIL, TRITICUM VULGARE (WHEAT) GERM OIL, PROPYLENE CARBONATE, STYRENE/BUTADIENE COPOLYMER, TITANIUM DIOXIDE(CI 77891), IRON OXIDES (CI 77492), IRON OXIDES (CI 77491), IRON OXIDES (CI 77499).

Questions or comments?

1-212-244-5170 info@amora.beauty